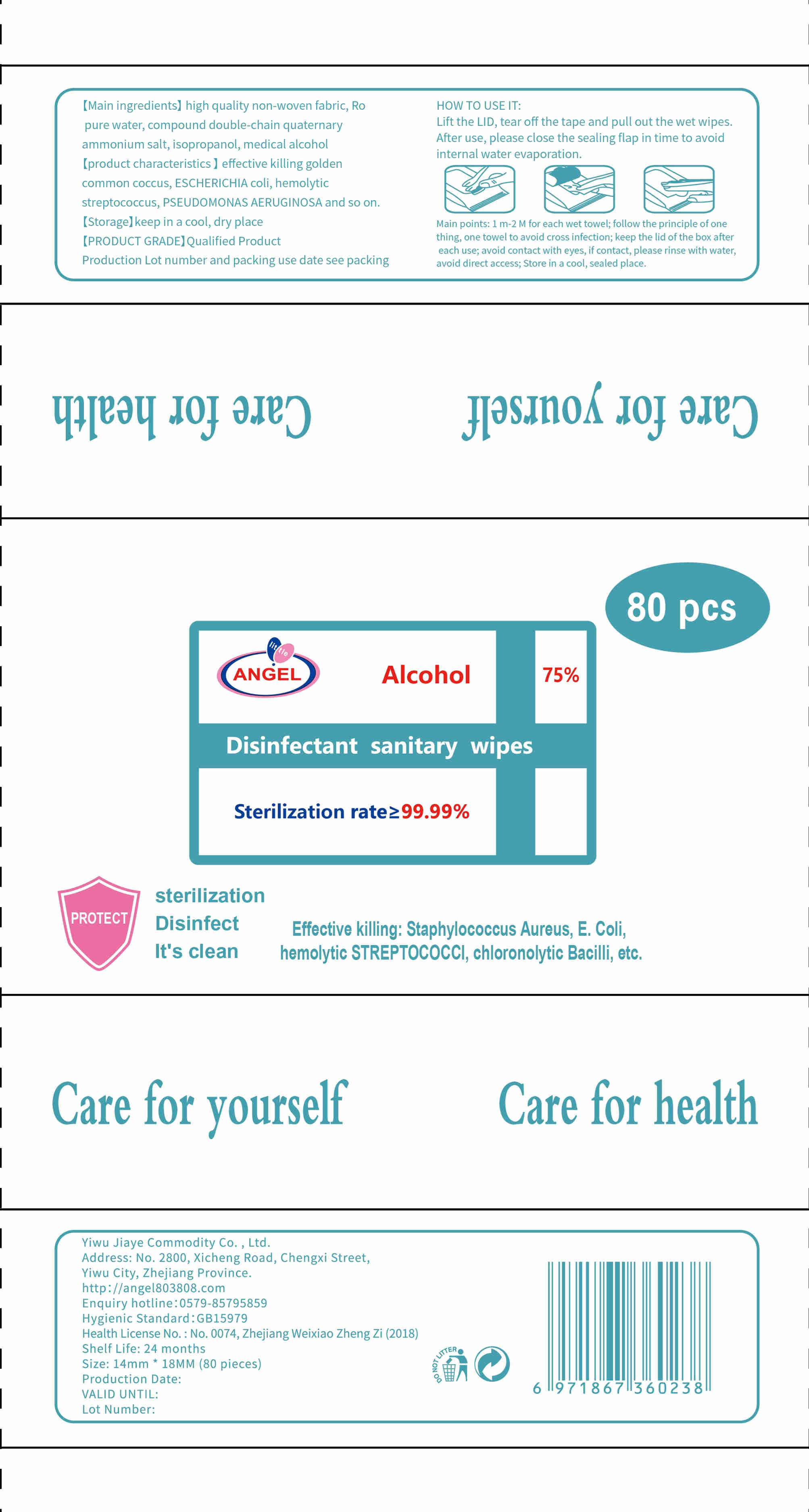 DRUG LABEL: Disinfectant sanitary wipes
NDC: 55473-001 | Form: CLOTH
Manufacturer: Yiwu Jiaye Commodity Co., Ltd.
Category: otc | Type: HUMAN OTC DRUG LABEL
Date: 20200601

ACTIVE INGREDIENTS: ALCOHOL 255 mL/80 1
INACTIVE INGREDIENTS: WATER

DOSAGE AND ADMINISTRATION

keep in a cool, dry place .

INACTIVE INGREDIENT

Non Woven Fabric

water

INDICATIONS AND USAGE

Lift the LID, tear off the tape and pull out the wet wipes.After use, please close the sealing flap in time to avoid internal water evaporation.

ACTIVE INGREDIENT

alcohol

keep out of reach of children

PURPOSE

Disinfection
Sterilization
No Rinseing

WARNINGS

1 m-2 M for each wet towel; follow the principle of one thing, one towel to avoid cross infection; keep the lid of the box after each use; avoid contact with eyes, if contact, please rinse with water,avoid direct access; Store in a cool, sealed place.